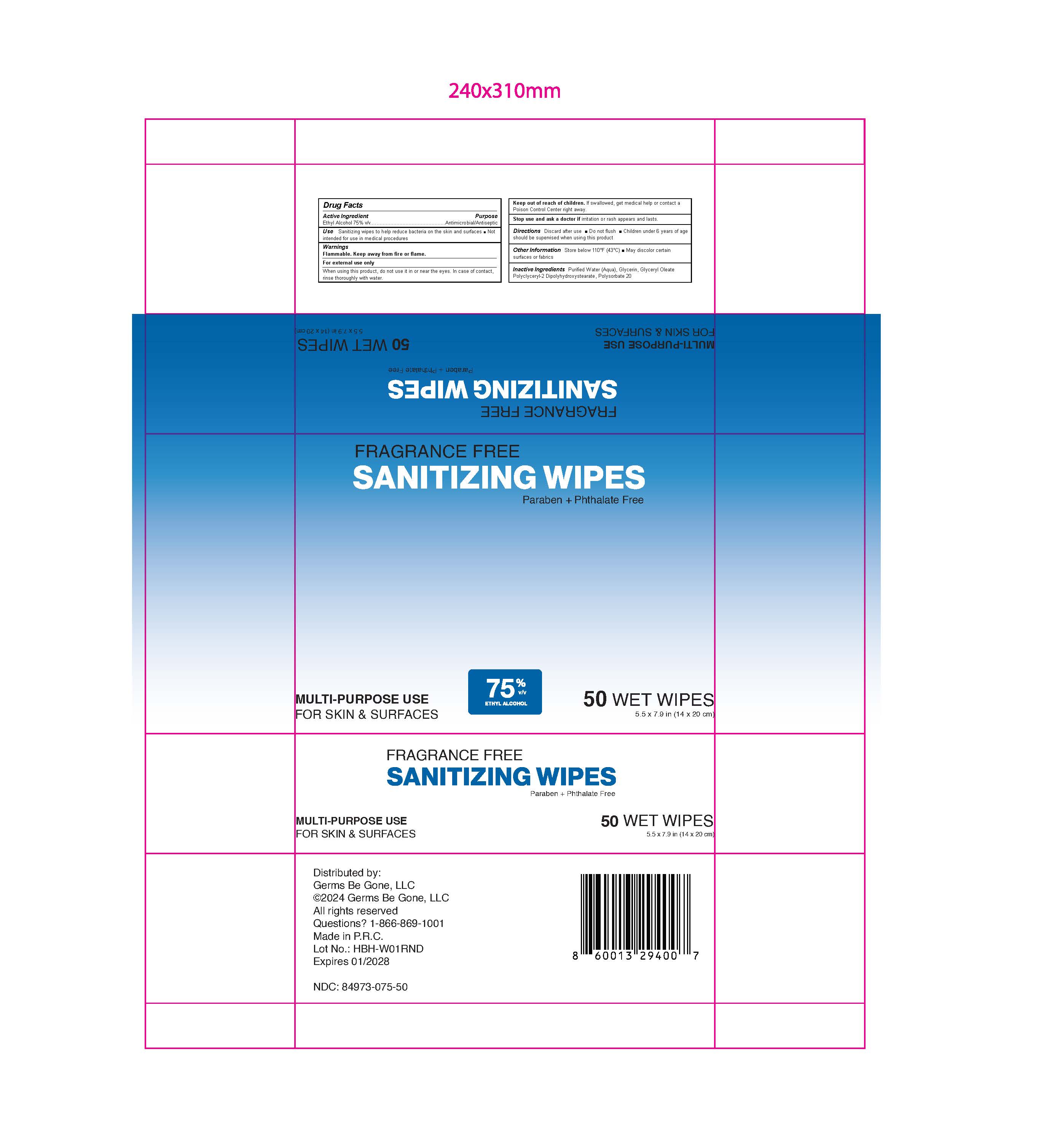 DRUG LABEL: Hand Sanitizing Wipes
NDC: 84973-0075 | Form: LIQUID
Manufacturer: Germs Be Gone LLC
Category: otc | Type: HUMAN OTC DRUG LABEL
Date: 20260120

ACTIVE INGREDIENTS: ALCOHOL 75 mL/100 mL
INACTIVE INGREDIENTS: POLYSORBATE 20; GLYCERIN; POLYGLYCERYL-2 DIPOLYHYDROXYSTEARATE; WATER

ACTIVE INGREDIENT

Alcohol 75% v/v. Purpose: Antimicrobial/Antiseptic

PURPOSE

Sanitizing wipes to help reduce bacteria on the skin and surfaces

Not intended for use in medical procedures

INDICATIONS AND USAGE

Sanitizing wipes to help reduce bacteria on skin. Not intended for use in medical procedures. Recommended for frequent use.

WARNINGS

Flammable. Keep away from fire or flame.

WARNINGS AND PRECAUTIONS

For external use only

When using this product, do not use it in or near the eyes. In case of contact, rinse eyes thoroughly with water.

Keep out of reach of children. If swallowed, get medical help or contact a Poison Control Center right away.

Stop use and ask a doctor if irritation or rash appears and lasts.

DOSAGE AND ADMINISTRATION

Discard after use

Do not flush

Children under 6 years of age should be supervised when using this product.

STORAGE AND HANDLING

Store below 110°F (43°C)
May discolor certain surfaces and fabrics

INACTIVE INGREDIENT

Purified Water (Aqua), Glycerin, Glyceryl Oleate, Polyglyceryl-2 Dipolyhydroxystearate, Polysorbate 20